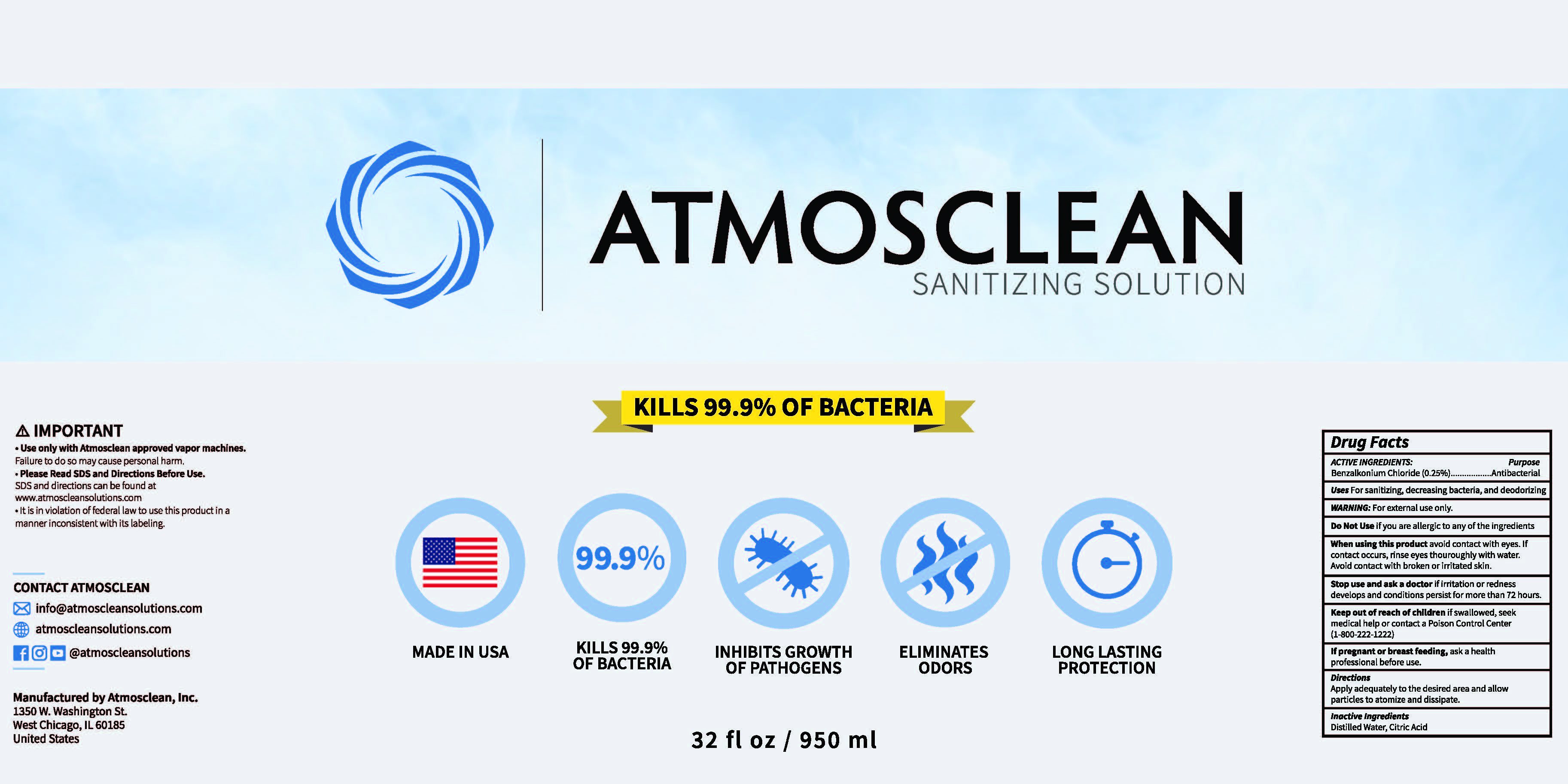 DRUG LABEL: ATMOSCLEAN SANITIZING
NDC: 79424-100 | Form: SOLUTION
Manufacturer: ATMOSCLEAN, INC.
Category: otc | Type: HUMAN OTC DRUG LABEL
Date: 20200714

ACTIVE INGREDIENTS: BENZALKONIUM CHLORIDE 0.25 g/100 mL
INACTIVE INGREDIENTS: CITRIC ACID MONOHYDRATE; WATER

Atmosclean Sanitizing Solution

ACTIVE INGREDIENT

Benzalkonium Chloride 0.25%

PURPOSE

Antibacterial

INDICATIONS AND USAGE

For sanitizing, decreasing bacteria, and deodorizing.

WARNINGS

For external use only.

DO NOT USE

if you are allergic to any of the ingredients.

WHEN USING

avoid contact with eyes. If contact occurs, rinse eyes thoroughly with water. avoid contact with broken or irritated skin.

STOP USE

if irritation or redness develops and conditions persist for more than 72 hours.

KEEP OUT OF REACH OF CHILDREN

if swallowed, seek medical help or contact a Poison Control Center (1-800-222-1222).

PREGNANCY OR BREAST FEEDING

ask a health professional before use.

DOSAGE AND ADMINISTRATION

Apply adequately to the desired area and allow particles to atomize and dissipate.

INACTIVE INGREDIENT

Distilled Water, Citric Acid